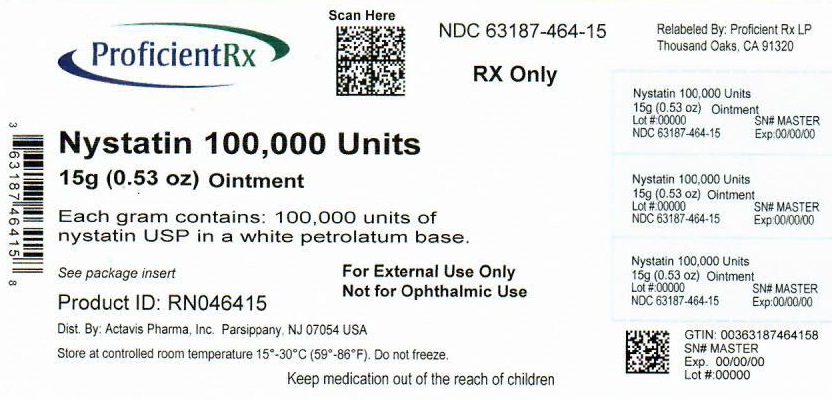 DRUG LABEL: Nystatin
NDC: 63187-464 | Form: OINTMENT
Manufacturer: Proficient Rx LP
Category: prescription | Type: HUMAN PRESCRIPTION DRUG LABEL
Date: 20221001

ACTIVE INGREDIENTS: NYSTATIN 100000 [USP'U]/1 g
INACTIVE INGREDIENTS: PETROLATUM

NYSTATIN OINTMENT USP
(100,000 units/g)

Rx Only

DESCRIPTION

Each gram of Nystatin Ointment USP contains 100,000 units of nystatin in a white petrolatum base.

CLINICAL PHARMACOLOGY

Nystatin is an antifungal antibiotic which is both fungistatic and fungicidal in vitro, against a wide variety of yeasts and yeast-like fungi. It probably acts by binding to sterols in the cell membrane of the fungus with a resultant change in membrane permeability allowing leakage of intracellular components. Nystatin is a polyene antibiotic of undetermined structural formula that is obtained from Streptomyces noursei, and is the first well tolerated antifungal antibiotic of dependable efficacy for the treatment of cutaneous, oral and intestinal infections caused by Candida (Monilia) albicans and other Candida species. It exhibits no appreciable activity against bacteria.

Nystatin provides specific therapy for all localized forms of candidiasis. Symptomatic relief is rapid, often occurring within 24 to 72 hours after the initiation of treatment. Cure is effected both clinically and mycologically in most cases of localized candidiasis.

INDICATIONS AND USAGE

Nystatin Ointment USP is indicated in the treatment of cutaneous or mucocutaneous mycotic infections caused by Candida (Monilia) albicans and other Candida species.

CONTRAINDICATIONS

Nystatin Ointment USP is contraindicated in patients with a history of hypersensitivity to any of its components.

PRECAUTIONS

Should a reaction of hypersensitivity occur the drug should be immediately withdrawn and appropriate measures taken.

ADVERSE REACTIONS

Nystatin is virtually nontoxic and nonsensitizing and is well tolerated by all age groups including debilitated infants, even on prolonged administration.

If irritation on topical application should occur, discontinue medication.

DOSAGE AND ADMINISTRATION

Nystatin Ointment USP should be applied liberally to the affected areas twice a day or as indicated until healing is complete. The ointment does not stain the skin or mucous membranes and it provides a simple, convenient means of treatment.

HOW SUPPLIED

Nystatin Ointment USP 100,000 units/g

15 g tube (0.53 oz)

Store at controlled room temperature 15°-30°C (59°-86°F). Do not freeze.

Distributed by:

Actavis Pharma, Inc.

Parsippany, NJ 07054 USA

FORM NO. 0166

Rev. 10/19

VC2752

Relabeled By:

Proficient Rx LP

Thousand Oaks, CA 91320